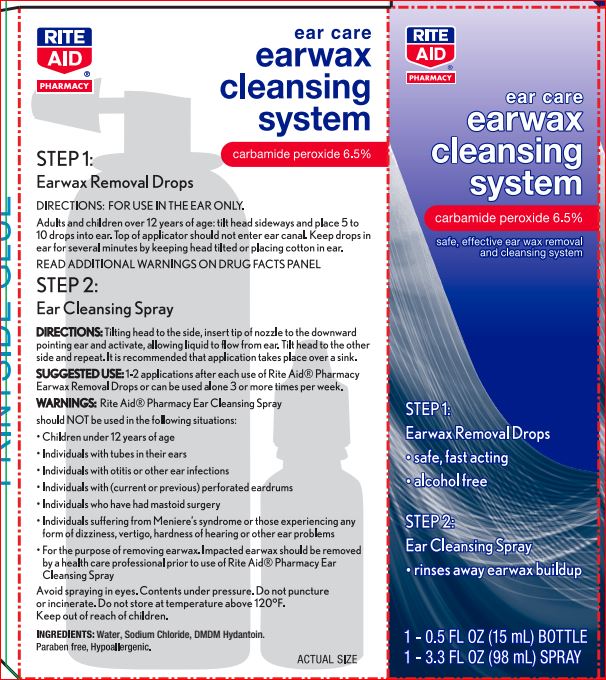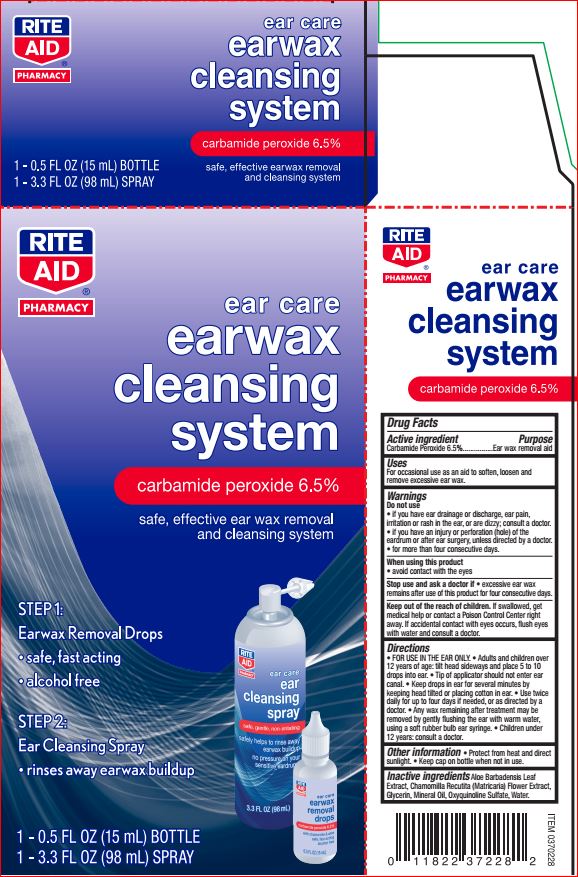 DRUG LABEL: Ear Wax Removal System
NDC: 11822-1225 | Form: KIT | Route: TOPICAL
Manufacturer: Rite Aid
Category: otc | Type: HUMAN OTC DRUG LABEL
Date: 20180613

ACTIVE INGREDIENTS: Carbamide Peroxide 6.5 g/100 mL
INACTIVE INGREDIENTS: ALOE VERA LEAF; CHAMOMILE; Glycerin; Oxyquinoline Sulfate; Mineral Oil; WATER

Drug Facts Kit

Active ingredient Purpose

Carbamide Peroxide - 6.50% Earwax removal aid

Uses

for occasional use as an aid to soften, loosen and remove excessive ear wax

Warnings For external use only

Keep out of reach of the children

If product is swallowed, get medical help or contact a Poison Control Center right away

Directions For use in the ear only. Adults and children over 12 years of age:

- tilt head sideways and place 5 to 10 drops into ear
- tip of applicator should not enter ear canal
- keep drops in ear for several minutes by keeping head tilted or placing cotton in the ear
- use twice daily for up to 4 days if needed, or as directed by a doctor
- any wax remaining after treatment may be removed by gently flushing the ear with warm water, using a soft rubber bulb ear syringe

Children under 12 years of age: consult a doctor.

Other information

• Protect from heat and direct sunlight • Keep cup on bottle when not in use

Inactive ingredient

Aloe Barbadensis Leaf Extract
Chamomilla Recutita (Matricaria) Flower Extract
Glycerin
Mineral Oil
Oxyquinoline Sulfate
Water